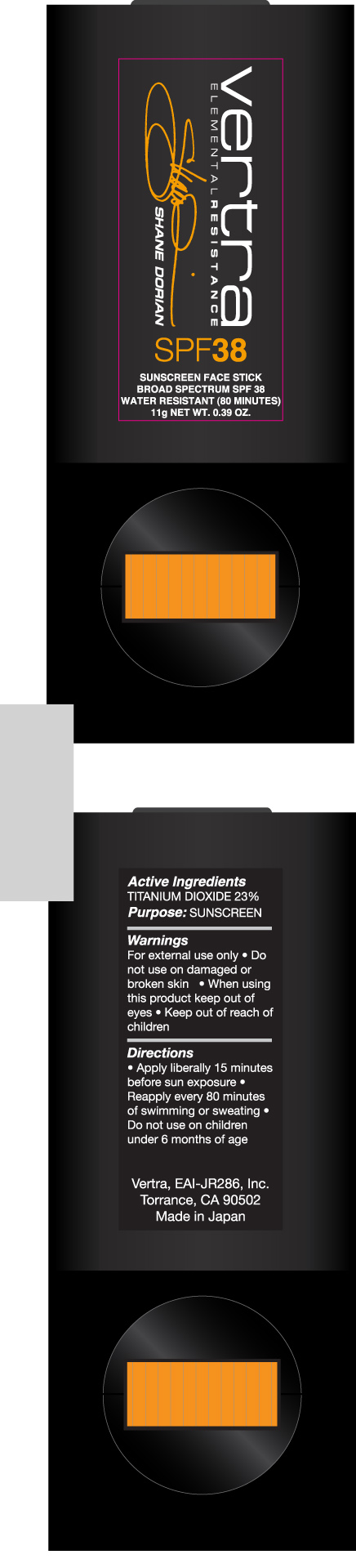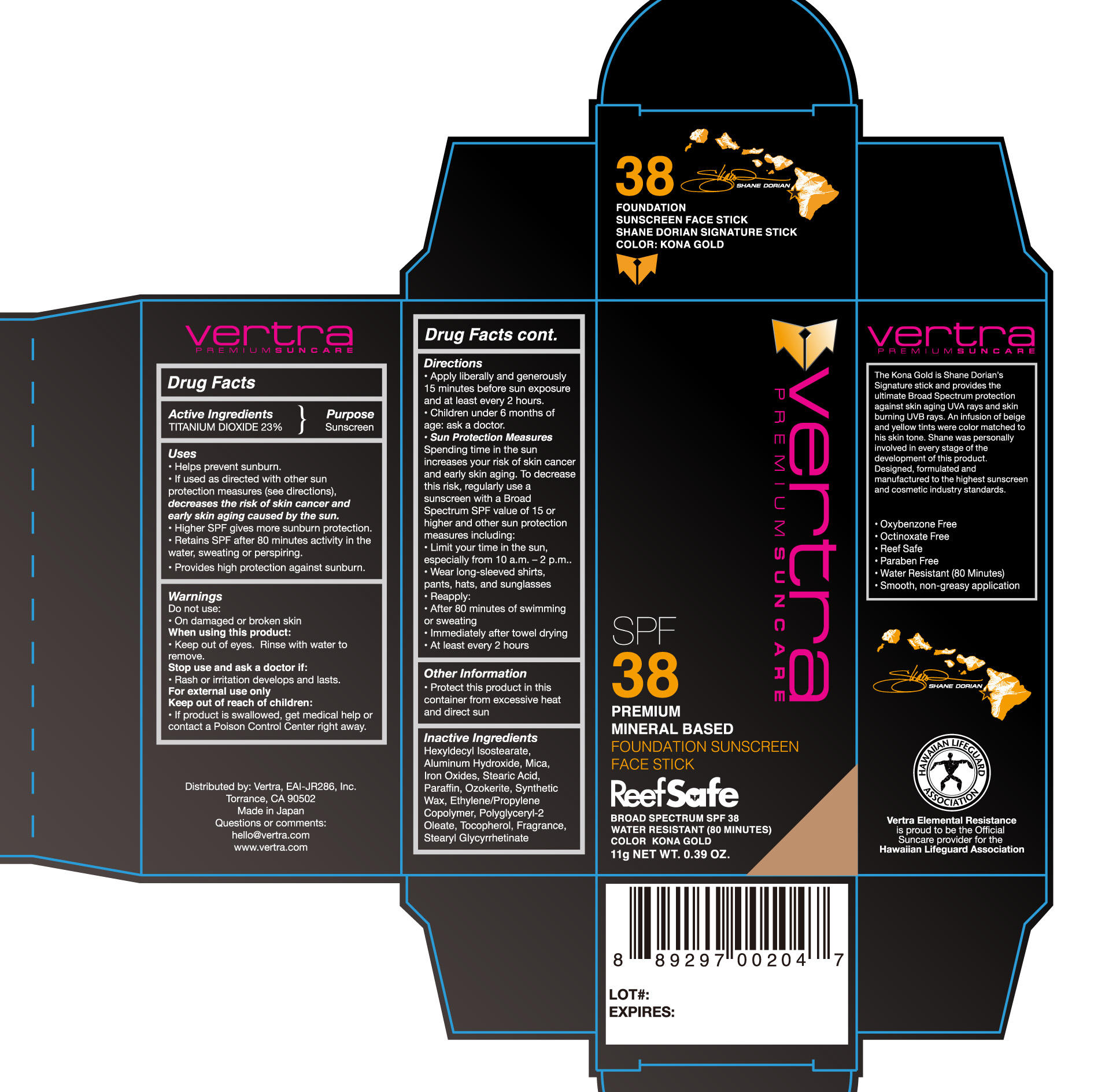 DRUG LABEL: Foundation Sunscreen Face Stick Broad Spectrum SPF 38 Kona Gold
NDC: 71014-024 | Form: STICK
Manufacturer: Eai-jr 286, Inc
Category: otc | Type: HUMAN OTC DRUG LABEL
Date: 20200708

ACTIVE INGREDIENTS: TITANIUM DIOXIDE 23 g/100 g
INACTIVE INGREDIENTS: ALUMINUM HYDROXIDE; HEXYLDECYL ISOSTEARATE; FERRIC OXIDE RED; FERRIC OXIDE YELLOW; FERROSOFERRIC OXIDE; MICA; CERESIN; PARAFFIN; STEARIC ACID; SYNTHETIC WAX (1200 MW); STEARYL GLYCYRRHETINATE

Foundation Sunscreen Face Stick Broad Spectrum SPF 38 Kona Gold

Active ingredients Purpose

Titanium Dioxide 23% Sunscreen

Uses

- helps prevent sunburn
- if used as directed with other sun protection measures (see directions), decreases the risk of skin cancer and early skin aging caused by the sun

Keep out of reach of children. If swallowed, get medical help or call a Poison Control Center right away.

Stop use and ask a doctor if rash or irritation develops and lasts.

WARNINGS

For external use only

Do not use on damaged or broken skin

When using this product keep out of eyes
Rinse with water to remove

Directions

- apply liberally and evenly 15 minutes before sun exposure
- apply to all skin exposed to sun
- use a water resistant sunscreen if swimming or sweating
- reapply: after 80 minutes of swimming or sweating
- immediately after towel drying
- at least every 2 hours
- Sun Protection Measures.
- spending time in the sun increases your risk of skin cancer and early skin aging. To decrease this risk, regularly use a sunscreen with a Broad Spectrum value 15 or higher and other sun protection measures including:
- limit time in the sun, especially from 10 a.m.-2p.m.
- wear long-sleeve shirts, pants, hats and sunglasses
- children under 6 months of age: ask a doctor

INACTIVE INGREDIENT

Hexyldecyl Isostearate, Aluminum Hydroxide, Mica, Iron Oxides, Stearic Acid, Paraffin, Ozokerite, Synthetic Wax, Ethylene/propylene copolymer, Polyglyceryl-2 Oleate, Tocopherol, fragrance, Stearyl Glycyrrhetinate

PACKAGE LABEL

Vertra Premium Suncare

SPF 38

Premium Mineral Based

Foundation Sunscreen Face Stick

Reef Safe

Broad Spectrum SPF 38

Water Resistant (80 minutes)

Color: Kona Gold

11g NET Wt. 0.39 oz